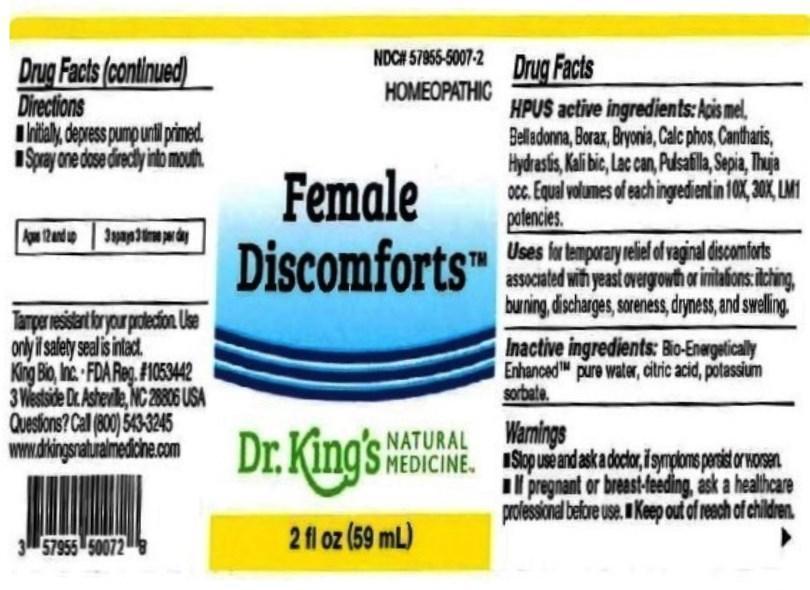 DRUG LABEL: Female Discomforts
NDC: 57955-5007 | Form: LIQUID
Manufacturer: King Bio Inc.
Category: homeopathic | Type: HUMAN OTC DRUG LABEL
Date: 20160624

ACTIVE INGREDIENTS: APIS MELLIFERA 10 [hp_X]/59 mL; ATROPA BELLADONNA 10 [hp_X]/59 mL; SODIUM BORATE 10 [hp_X]/59 mL; BRYONIA ALBA ROOT 10 [hp_X]/59 mL; TRIBASIC CALCIUM PHOSPHATE 10 [hp_X]/59 mL; LYTTA VESICATORIA 10 [hp_X]/59 mL; GOLDENSEAL 10 [hp_X]/59 mL; POTASSIUM DICHROMATE 10 [hp_X]/59 mL; CANIS LUPUS FAMILIARIS MILK 10 [hp_X]/59 mL; PULSATILLA PRATENSIS 10 [hp_X]/59 mL; SEPIA OFFICINALIS JUICE 10 [hp_X]/59 mL; THUJA OCCIDENTALIS LEAFY TWIG 10 [hp_X]/59 mL
INACTIVE INGREDIENTS: WATER; ANHYDROUS CITRIC ACID; POTASSIUM SORBATE

Female Discomforts™

ACTIVE INGREDIENT

Drug Facts__________________________________________________________________________________________________________

HPUS active ingredients: Apis mellifica, Belladonna, Borax, Bryonia, Calcarea phosphorica, Cantharis, Hydrastis canadensis, Kali bichromicum, Lac caninum, Pulsatilla, Sepia, Thuja occidentalis. Equal volumes of each ingredient in 10X, 30X, LM1 potencies.

INDICATIONS AND USAGE

Uses for temporary relief of vaginal discomforts associated with yeast overgrowth or irritations: itching, burning, discharges, soreness, dryness, and swelling.

Inactive Ingredients:

Bio-Energetically Enhanced™ pure water, citric acid and potassium sorbate.

Warnings

- Stop use and ask your doctor if symptoms persist or worsen.
- If pregnant or breast-feeding, ask a healthcare professional before use.

- Keep out of reach of children.

Directions

- Initially, depress pump until primed.
- Spray one dose directly into mouth.
- Ages 12 and up: 3 sprays 3 times per day.

OTHER SAFETY INFORMATION

Tamper resistant for your protection. Use only if seal is intact.

PURPOSE

Uses for temporary relief of vaginal discomforts associated with yeast overgrowth or irritations:

- itching
- burning
- discharges
- soreness
- dryness
- swelling